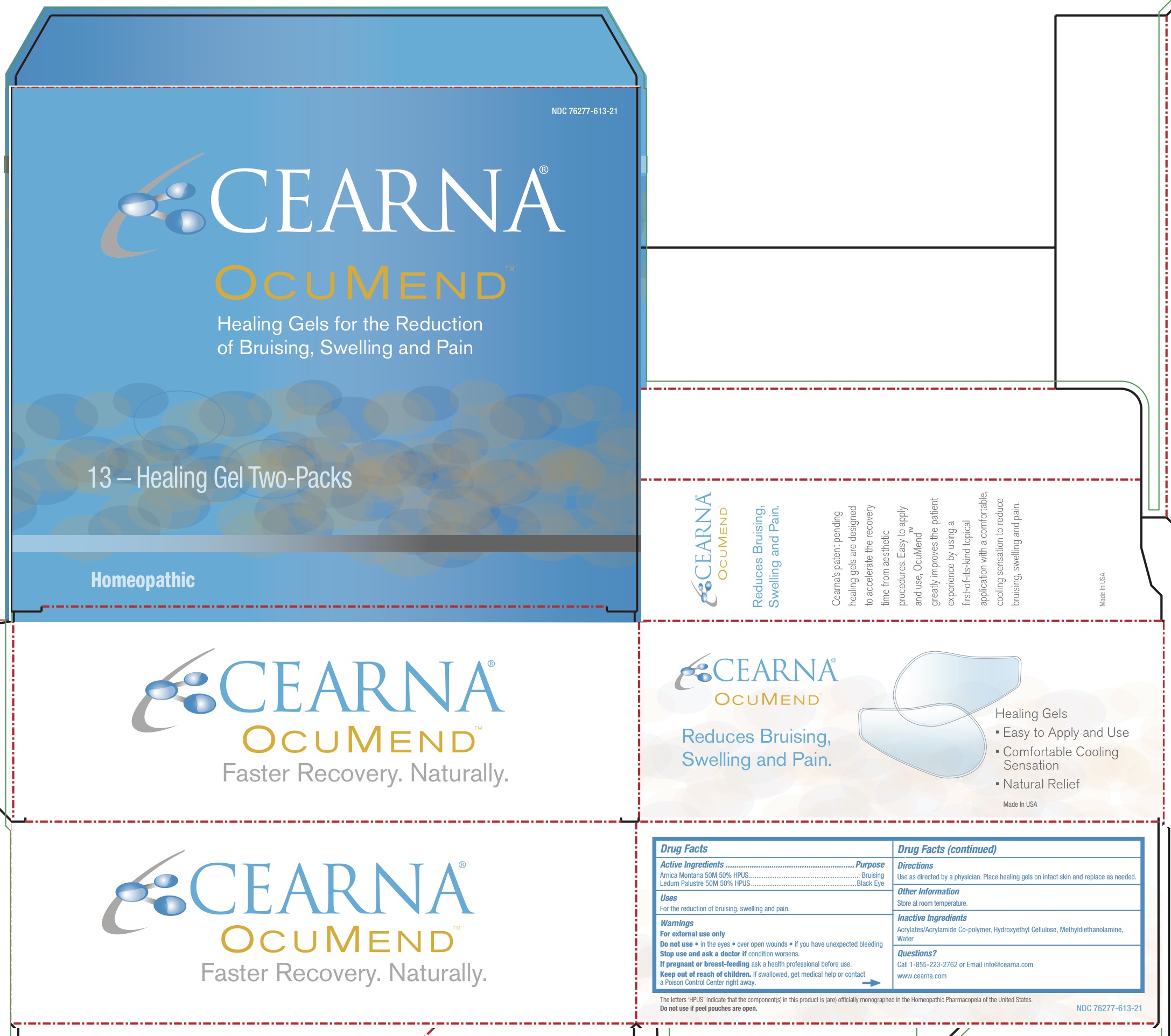 DRUG LABEL: OcuMend
NDC: 76277-613 | Form: PATCH
Manufacturer: Cearna, Inc.
Category: homeopathic | Type: HUMAN OTC DRUG LABEL
Date: 20160311

ACTIVE INGREDIENTS: ARNICA MONTANA 50 [hp_M]/1 1; LEDUM PALUSTRE TWIG 50 [hp_M]/1 1
INACTIVE INGREDIENTS: METHYL DIETHANOLAMINE; WATER

OcuMend Healing Gels

Active Ingredients

Arnica Montana 50M 50%
Ledum Palustre 50M 50%

Homeopathic Purpose

Arnica Montana 50M: Bruising
Ledum Palustre 50M: Black Eye

Uses

For the Reduction of Bruising, Swelling and Pain.

Warnings

- For external use only
- Do not use in the eyes, over open wounds, or if you have unexpected bleeding
- Stop use and ask a doctor if conditon worsens
- If pregnant or breast-feeding, ask a health professional before use.

- Keep out of reach of children.

Directions

Use as directed by a physician. Place healing gels on intact skin and replace as needed.

Other Information

Store at room temperature.

Inactive Ingredients

Acrylates/Acrylamide Co-polymer, Hydroxyethyl Cellulose, Methyldiethanolamine, Water

DESCRIPTION

The letters HPUS indicate that the component(s) in this product is (are) officially monographed in the Homeopathic Pharmacopeia of the United States.

Do not use if box seal is broken or missing or if peel pouches are open.

Questions? Ingredients

Call 1-855-223-2762 or Email: info@cearna.com